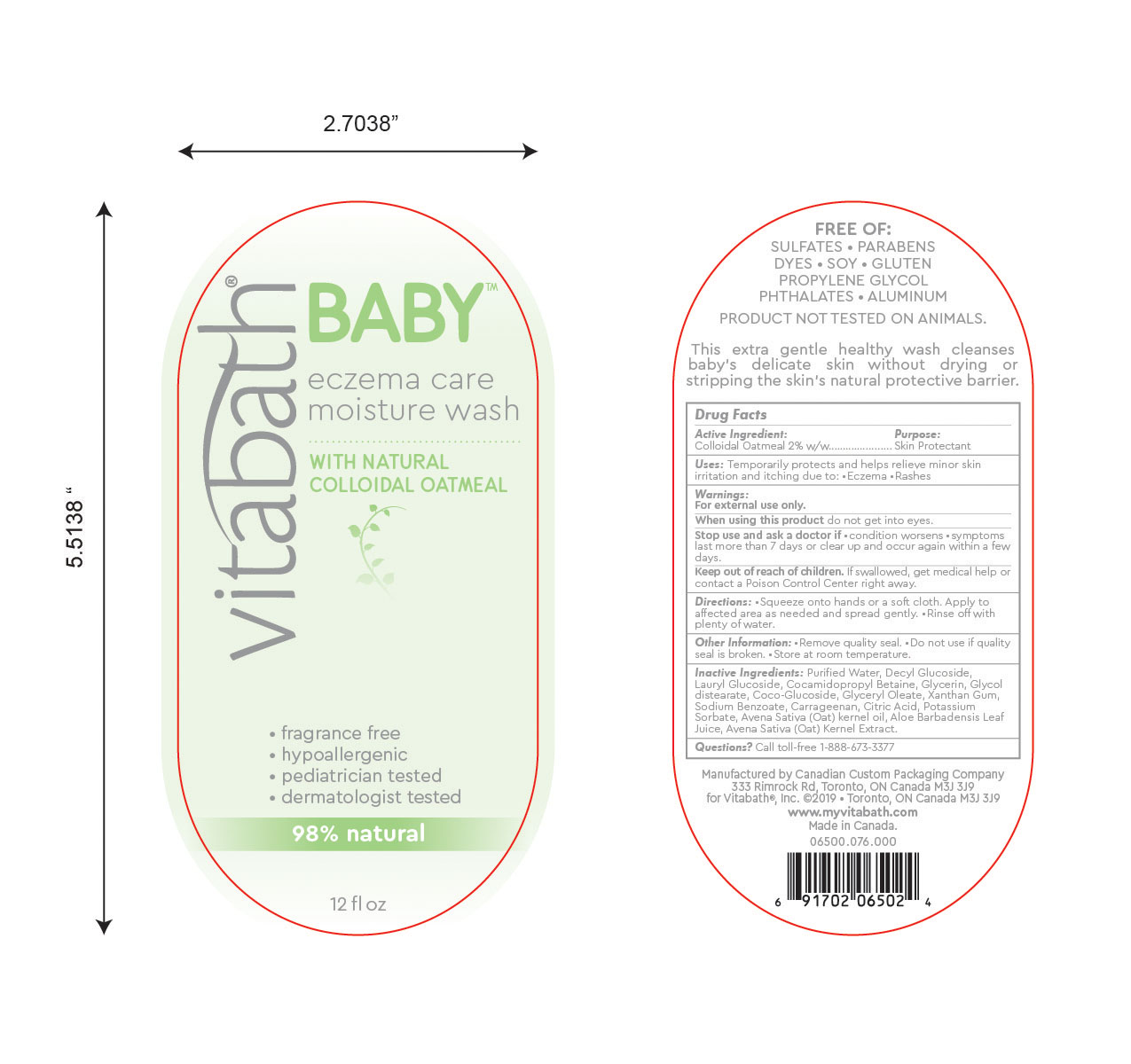 DRUG LABEL: Vitabath Baby Eczema Care Moisture Wash
NDC: 73172-002 | Form: LOTION
Manufacturer: Vitabath Inc.
Category: otc | Type: HUMAN OTC DRUG LABEL
Date: 20190611

ACTIVE INGREDIENTS: OATMEAL 2 g/100 g
INACTIVE INGREDIENTS: OAT KERNEL OIL; OAT; ANHYDROUS CITRIC ACID; POTASSIUM SORBATE; ALOE VERA LEAF; LAURYL GLUCOSIDE; SODIUM BENZOATE; WATER; DECYL GLUCOSIDE; COCAMIDOPROPYL BETAINE; CARRAGEENAN; GLYCERIN; GLYCOL DISTEARATE; COCO GLUCOSIDE; GLYCERYL OLEATE; XANTHAN GUM

Vitabath Baby Eczema Care Moisture Wash

Active Ingredient

Colloidal Oatmeal 2% w/w

Purpose

Skin protectant

Uses

Tempoarily protects and helps relieve minor skin irritation and itching due to •Eczema •Rashes

Warnings

For external use only.

When using this product

do not get into eyes.

STOP USE AND ASK A DOCTOR IF

- CONDITIONS WORSENS
- SYMPTOMS LAST MORE THAN 7 DAYS OR CLEAR UP AND OCCUR AGAIN WITHIN A FEW DAYS.

Keep out of reach of children. If swallowed get medical help or contact a Poison Control Center right away.

Directions:

•Squeeze onto hands or a soft cloth. Apply to affected area as needed and spread gently. •Rinse off with plenty of water.

OTHER INFORMATION:

•Remove quality seal. •Do not use if quality seal is broken. •Store at room temperature.

Inactive Ingredients:

Purified Water
Decyl Glucoside
Lauryl Glucoside
Cocamidopropyl Betaine
Glycerin
Glycol distearate
Coco-Glucoside
Glyceryl Oleate
Xanthan Gum
Sodium Benzoate
Carrageenan
Citric Acid
Potassium Sorbate
Avena Sativa (Oat) kernel oil
Aloe Barbadensis Leaf Juice
Avena Sativa (Oat) Kernel Extract

Questions? Call toll-free 1-888-673-3377